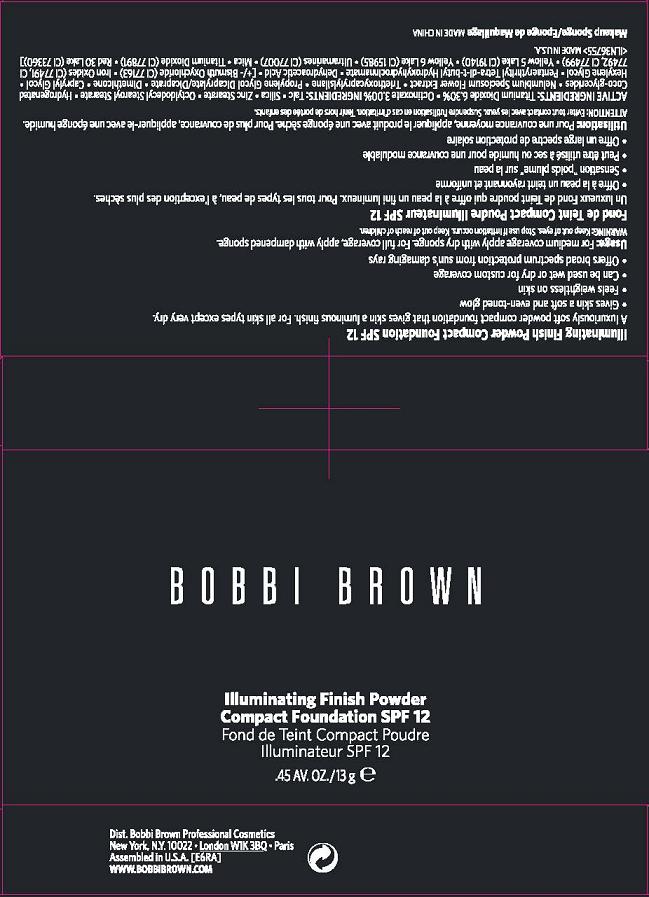 DRUG LABEL: ILLUMINATING FINISH 
NDC: 64141-007 | Form: POWDER
Manufacturer: Bobbi Brown Professional Cosmetics Inc.
Category: otc | Type: HUMAN OTC DRUG LABEL
Date: 20100901

ACTIVE INGREDIENTS: TITANIUM DIOXIDE 6.3 g/100 g; OCTINOXATE 3.0 g/100 g

ACTIVE INGREDIENT

ACTIVE INGREDIENTS: TITANIUM DIOXIDE 6.30% [] OCTINOXATE 3.00%

INACTIVE INGREDIENTS:

TALC [] SILICA [] ZINC STEARATE [] OCTYLDODECYL STEAROYL STEARATE [] HYDROGENATED COCO-GLYCERIDES [] NELUMBIUM SPECIOSUM FLOWER EXTRACT [] TRIETHOXYCAPRYLYLSILANE [] PROPYLENE GLYCOL DICAPRYLATE/DICAPRATE [] DIMETHICONE [] CAPRYLYL GLYCOL [] HEXYLENE GLYCOL [] PENTAERYTHRITYL TETRA-DI-T-BUTYL HYDROXYHYDROCINNAMATE [] DEHYDROACETIC ACID [] [+/- BISMUTH OXYCHLORIDE (CI 77163) [] IRON OXIDES (CI 77491, CI 77492, CI 77499) [] YELLOW 5 LAKE (CI 19140) [] YELLOW 6 LAKE (CI 15985) [] TITANIUM DIOXIDE (CI 77891) [] MICA [] RED 30 LAKE (CI 73360)]

WHEN USING

DIRECTIONS: FOR MEDIUM COVERAGE APPLY WITH DRY SPONGE. FOR FULL COVERAGE APPLY WITH DAMPENED SPONGE.

WARNINGS

WARNING: KEEP OUT OF EYES. STOP IF IRRITATION OCCURS. KEEP OUT OF REACH OF CHILDREN.

PACKAGE LABEL

PRINCIPAL DISPLAY PANEL:

BOBBI BROWN
ILLUMINATING FINISH POWDER
COMPACT FOUNDATION SPF 12
0.45 OZ/13 g
DIST. BOBBI BROWN PROFESSIONAL COSMETICS INC
NEW YORK, NY 10022